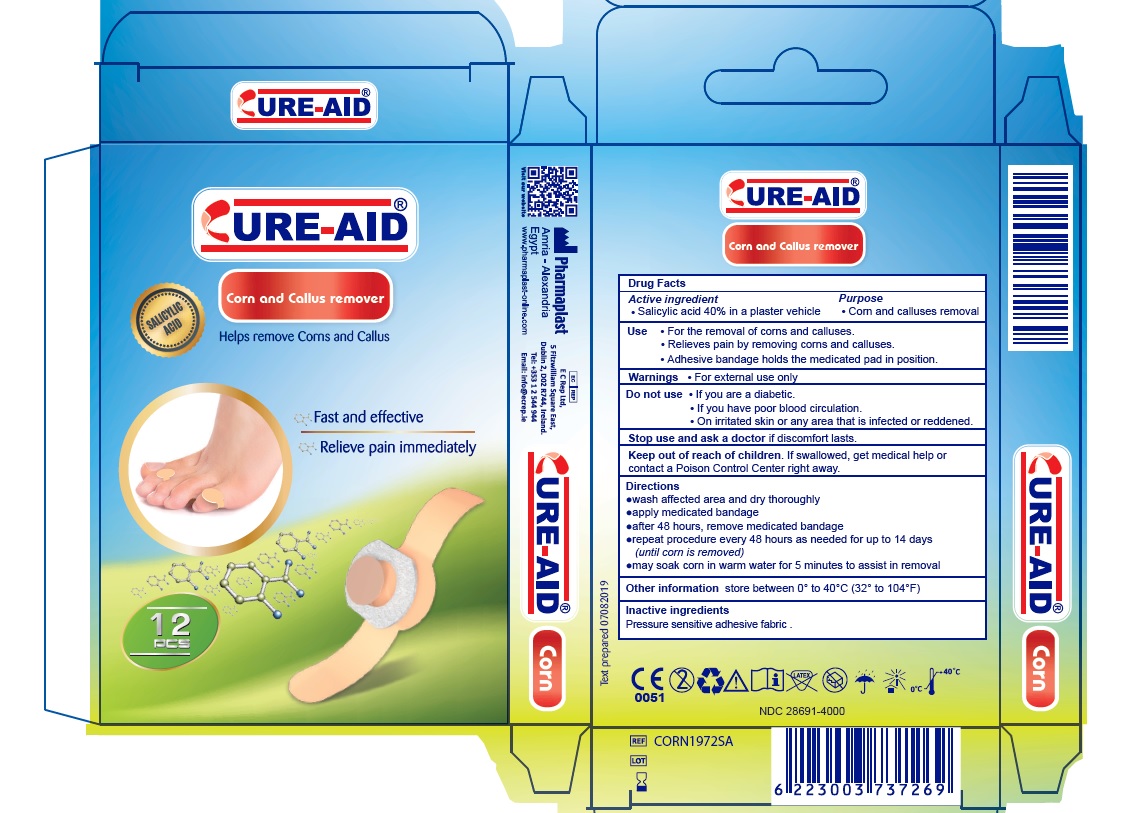 DRUG LABEL: Cure-Aid Corn Plasters
NDC: 28691-4000 | Form: PATCH
Manufacturer: Pharmaplast SAE
Category: otc | Type: HUMAN OTC DRUG LABEL
Date: 20250107

ACTIVE INGREDIENTS: SALICYLIC ACID 40 mg/1 1
INACTIVE INGREDIENTS: LOW DENSITY POLYETHYLENE; VINYL ACETATE

Corn and Callus remover

Active ingredient

- Salicylic acid 40% in a plaster vehicle

Purpose

- Corn and calluses removal

Use

- For the removal of corns and calluses.
- Relieves pain by removing corns and calluses.
- Adhesive bandage holds the medicated pad in position.

Warnings

- For External Use Only

Do not use

- If you are a diabetic.
- If you have poor blood circulation.
- On irritated skin or any area that is infected or reddened.

Stop use and ask a doctor if discomfort lasts.

Keep out of reach of children. If swallowed, get medical help or contact a Poison Control Center right away.

Directions

- wash affected area and dry thoroughly
- apply medicated bandage
- after 48 hours, remove medicated bandage
- repeat procedure every 48 hours as needed for up to 14 days (until corn is removed)
- may soak corn in warm water for 5 minutes to assist in removal

Other information

store between 0º to 40ºC (32º to 104ºF)

Inactive ingredients

Pressure sensitive adhesive fabric.

CURE-AID®

Corn and Callus remover

Helps remove Corns and Callus

Fast and effective

Relieve pain immediately

Pharmaplast
Amria – Alexandria
Egypt
www.Pharmaplast-online.com